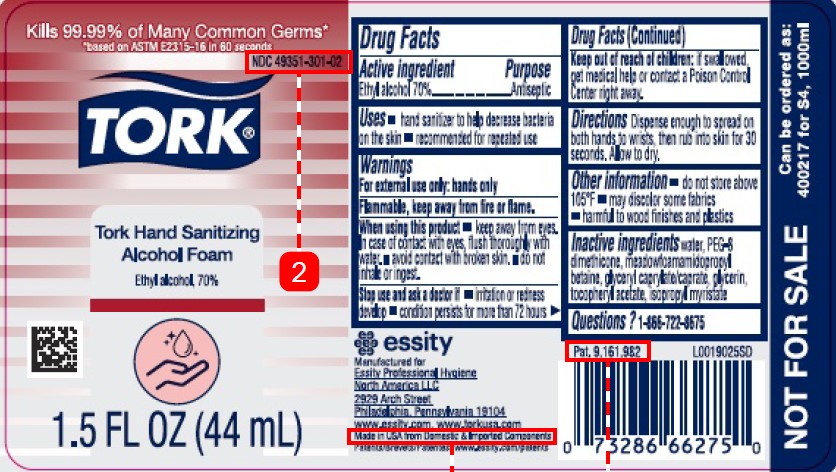 DRUG LABEL: Tork Hand Sanitizing Alcohol Foam
NDC: 49351-301 | Form: LIQUID
Manufacturer: Essity Professional Hygiene North America LLC
Category: otc | Type: HUMAN OTC DRUG LABEL
Date: 20260204

ACTIVE INGREDIENTS: ALCOHOL 70 mL/100 mL
INACTIVE INGREDIENTS: WATER; PEG-8 DIMETHICONE; MEADOWFOAMAMIDOPROPYL BETAINE; GLYCERYL CAPRYLATE/CAPRATE; GLYCERIN; .ALPHA.-TOCOPHEROL ACETATE; ISOPROPYL MYRISTATE

Tork_Essity 456.002/456AC
70% Alcohol Foaming Hand Sanitizer

Active ingredient

Ethyl alcohol 70%

Purpose

Antiseptic

Uses

- hand sanitizer to help decrease bacteria on the skin
- recommended for repeated use

Warnings

For external use only: hands only

Flammable, keep away from fire or flame.

When using this product

- keep out of eyes. In case of contact with eyes, flush thoroughly with water.
- avoid contact with broken skin
- do not inhale or ingest

Stop use and ask a doctor if

- irritation or redness develop
- condition persists for more than 72 hours.

Keep out of reach children

If swallowed, get medical help or contact a Poison Control Center right away.

Directions

Dispense enough to spread on both hands to wrists, then rub into skin for at least 30 seconds. Allow to dry.

Other information

- do not store above 105° F
- may discolor some fabrics
- harmful to wood finishes and plastics

Inactive ingredients

water, PEG-8 Dimethicone, meadowfoamamidopropyl betaine, glyceryl caprylate/caprate, glycerin, tocopheryl acetate, isopropyl myristate

Questions?

1-866-722-8675

essity

Manufactured for

Essity Professional Hygiene

North America LLC

2929 Arch Street

Philadelphia, Pennsylvania 19104

www.essity.com, www.torkusa.com

Made in USA of Domestic and Imported Compnents

Patents/Brevets/Patentes: www.essity.com/patents

Pat.9.161.982

NOT FOR SALE

Can be ordered as:

400217 for S4, 1000ml

Principal display panel

Kills 99.99% of Many Common Germs*

*based on ASTM E2315-16 in 60 seconds

NDC 49351-301-02

TORK®

Tork Hand Sanitizing

Alcohol Foam

Ethyl alcohol, 70%

1.5 FL OZ (44mL)